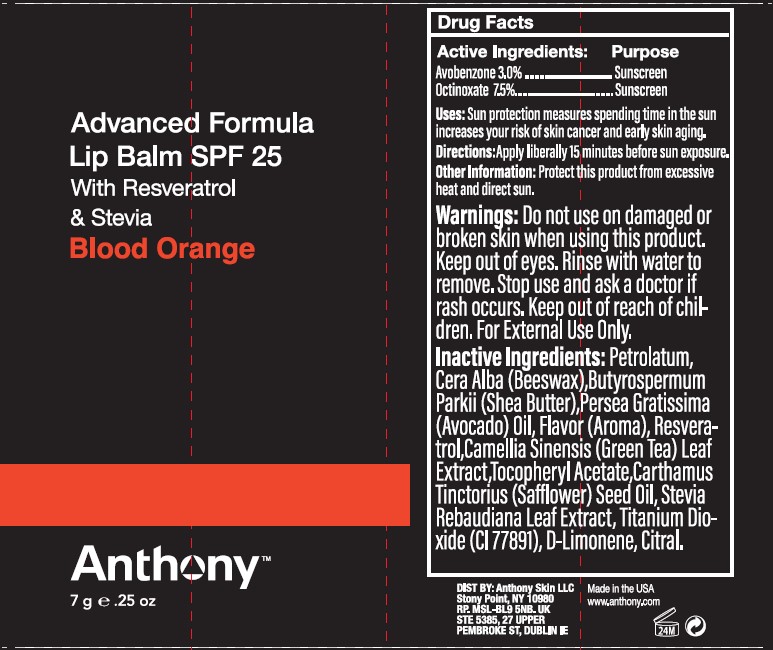 DRUG LABEL: Advanced Formula Lip Balm SPF 25
NDC: 80949-002 | Form: CREAM
Manufacturer: Anthony Skin LLC
Category: otc | Type: HUMAN OTC DRUG LABEL
Date: 20250112

ACTIVE INGREDIENTS: AVOBENZONE 3 g/100 g; OCTINOXATE 7.5 g/100 g
INACTIVE INGREDIENTS: PETROLATUM; YELLOW WAX; SHEA BUTTER; AVOCADO OIL; SAFFLOWER OIL; TITANIUM DIOXIDE; STEVIA REBAUDIANA LEAF; .ALPHA.-TOCOPHEROL ACETATE; RESVERATROL; GREEN TEA LEAF; LIMONENE, (+)-; CITRAL

Advanced Formula Lip Balm SPF 25

Active Ingredients:

Avobenzone 3.0%
Octinoxate 7.5%

Purpose

Sunscreen

Uses:

Sun protection measures spending time in the sun increases your risk of skin cancer and early skin aging.

Directions:

Apply liberally 15 minutes before sun exposure.

Other Information:

Protect this product from excessive heat and direct sun.

Warnings:

Do not use

on damaged or broken skin when using this product. Keep out of eyes. Rinse with water to remove.

Stop use

and ask a doctor if rash occurs.

Keep out of reach of children.

For External Use Only.

Inactive Ingredients:

Petrolatum, Cera Alba (Beeswax), Butyrospermum Parkii (Shea Butter), Persea Gratissima (Avocado) Oil, Flavor (Aroma), Resveratrol, Camellia Sinensis (Green Tea) Leaf Extract, Tocopheryl Acetate, Carthamus Tinctorius (Safflower) Seed Oil, Stevia Rebaudiana Leaf Extract, Titanium Dioxide (CI 77891), D-Limonene, Citral.

Principal Display Panel

Advanced Formula
Lip Balm SPF 25
With Resveratrol
& Stevia
Blood Orange

Anthony™

7 g ℮ .25 oz
DIST BY: Anthony Skin LLC
Stony Point, NY 10980
RP. MSL-BL9 5NB. UK
STE 5385, 27 UPPER
PEMBROKE ST, DUBLIN IE
Made in the USA
www.anthony.com

Label